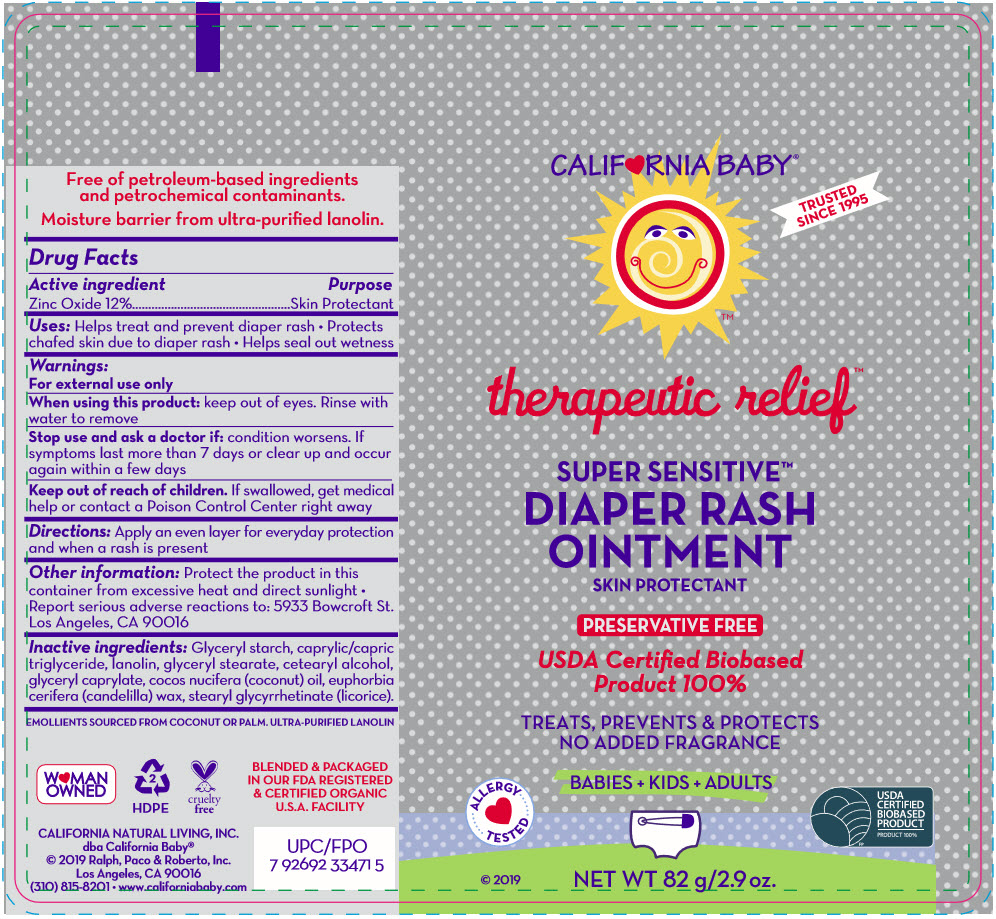 DRUG LABEL: SUPER SENSITIVE DIAPER RASH
NDC: 52915-140 | Form: CREAM
Manufacturer: ORGANIC & SUSTAINABLE BEAUTY
Category: otc | Type: HUMAN OTC DRUG LABEL
Date: 20241108

ACTIVE INGREDIENTS: ZINC OXIDE 120 mg/1 g
INACTIVE INGREDIENTS: DIMETHYLIMIDAZOLIDINONE RICE STARCH; MEDIUM-CHAIN TRIGLYCERIDES; lanolin; glyceryl stearate SE; CETOSTEARYL ALCOHOL; GLYCERYL MONOCAPRYLATE; COCONUT OIL; CANDELILLA WAX; stearyl glycyrrhetinate

SUPER SENSITIVE™ DIAPER RASH OINTMENT

Drug Facts

Active ingredient

Zinc Oxide 12%

Purpose

Skin Protectant

Uses

Helps treat and prevent diaper rash

- Protects chafed skin due to diaper rash
- Helps seal out wetness

Warnings

For external use only

When using this product: keep out of eyes. Rinse with water to remove

Stop use and ask a doctor if: condition worsens. If symptoms last more than 7 days or clear up and occur again within a few days

Keep out of reach of children. If swallowed, get medical help or contact a Poison Control Center right away

Directions

Apply an even layer for everyday protection and when a rash is present

Other information

Protect the product in this container from excessive heat and direct sunlight

- Report serious adverse reactions to: 5933 Bowcroft St. Los Angeles, CA 90016

Inactive ingredients

Glyceryl starch, caprylic/capric triglyceride, lanolin, glyceryl stearate, cetearyl alcohol, glyceryl caprylate, cocos nucifera (coconut) oil, euphorbia cerifera (candelilla) wax, stearyl glycyrrhetinate (licorice).

PRINCIPAL DISPLAY PANEL - 82 g Tube Label

CALIF♥RNIA BABY®

TRUSTED
SINCE 1995

therapeutic relief™

SUPER SENSITIVE™
DIAPER RASH
OINTMENT
SKIN PROTECTANT

PRESERVATIVE FREE

USDA Certiﬁed Biobased
Product 100%

TREATS, PREVENTS & PROTECTS
NO ADDED FRAGRANCE

BABIES + KIDS + ADULTS

ALLERGY
TESTED

© 2019

NET WT 82 g/2.9 oz.

USDA
CERTIFIED
BIOBASED
PRODUCT
PRODUCT 100%